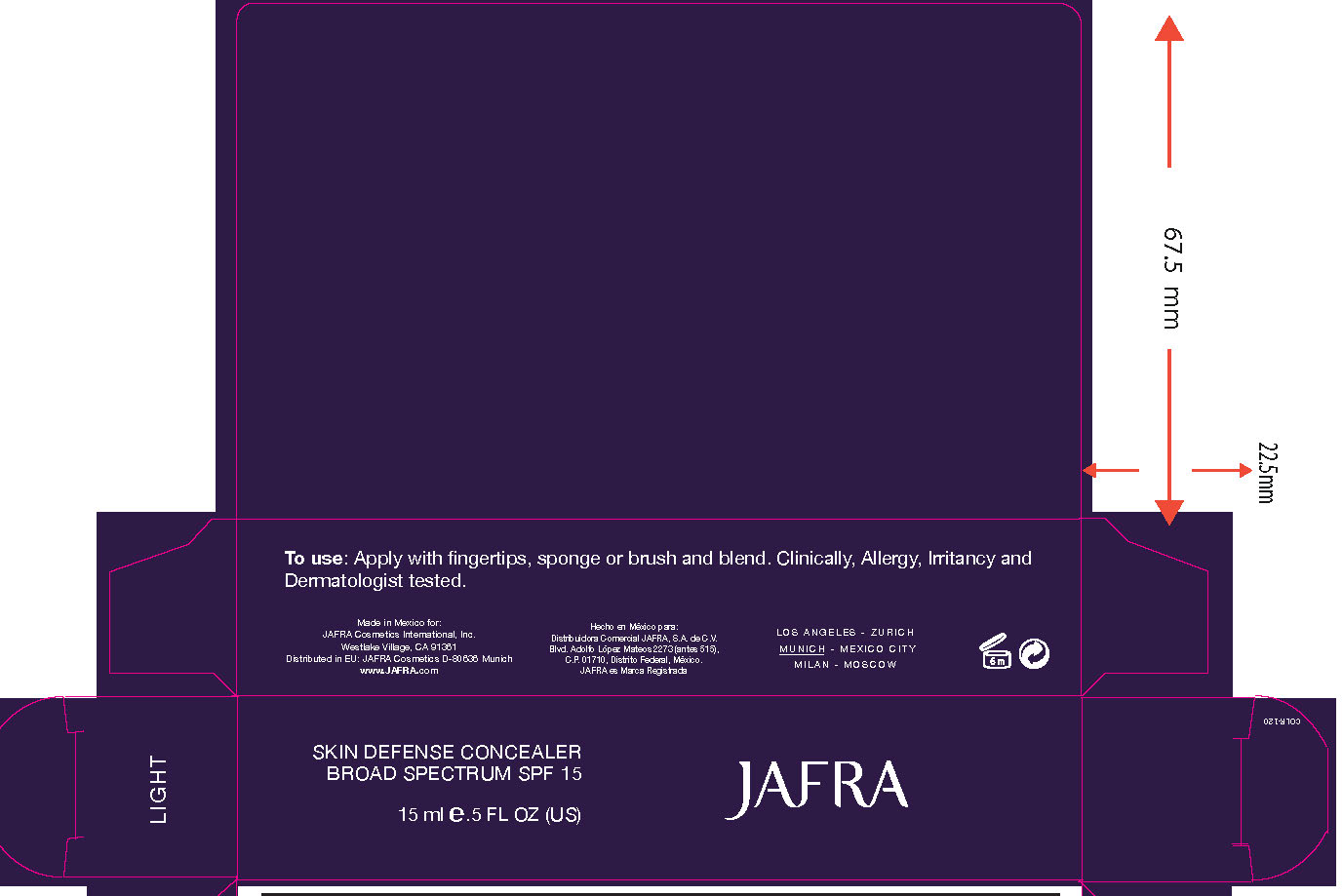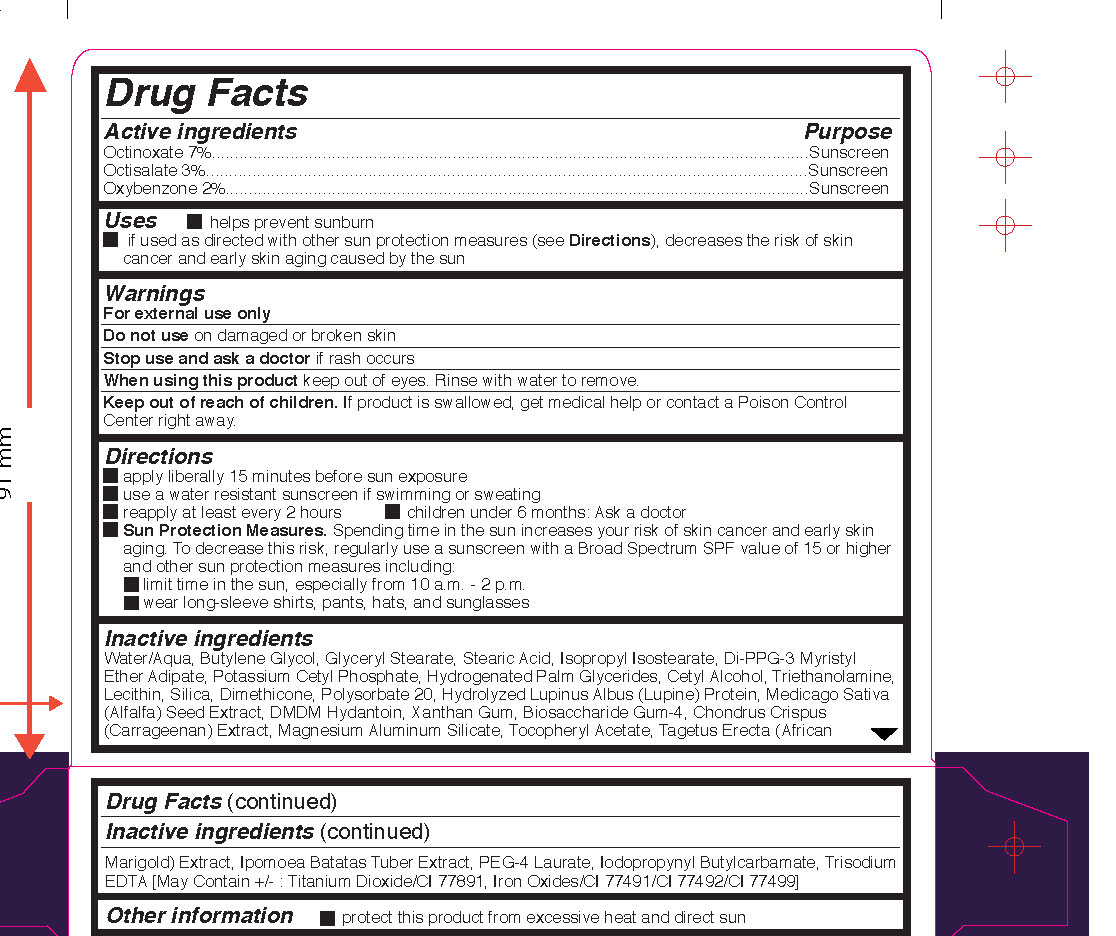 DRUG LABEL: Light Skin Defense Concealer Broad Spectrum SPF 15




NDC: 68828-170 | Form: CREAM
Manufacturer: Jafra Cosmetics International Inc
Category: otc | Type: HUMAN OTC DRUG LABEL
Date: 20240105

ACTIVE INGREDIENTS: OCTINOXATE 7 g/100 mL; OCTISALATE 3 g/100 mL; OXYBENZONE 2 g/100 mL
INACTIVE INGREDIENTS: WATER; BUTYLENE GLYCOL; GLYCERYL MONOSTEARATE; STEARIC ACID; ISOPROPYL ISOSTEARATE; DI-PPG-3 MYRISTYL ETHER ADIPATE; POTASSIUM CETYL PHOSPHATE; HYDROGENATED PALM GLYCERIDES; CETYL ALCOHOL; TROLAMINE; LECITHIN, SOYBEAN; SILICON DIOXIDE; DIMETHICONE; POLYSORBATE 20; ALFALFA SEED; DMDM HYDANTOIN; XANTHAN GUM; CHONDRUS CRISPUS; MAGNESIUM ALUMINUM SILICATE; .ALPHA.-TOCOPHEROL ACETATE; SWEET POTATO; PEG-4 LAURATE; IODOPROPYNYL BUTYLCARBAMATE; EDETATE TRISODIUM; TITANIUM DIOXIDE; FERRIC OXIDE RED; FERRIC OXIDE YELLOW; FERROSOFERRIC OXIDE

Skin Defense Concealer SPF 15

Active Ingredients Purpose

Octinoxate 7% Sunscreen

Octisalate 3% Sunscreen

Oxybenzone 2% Sunscreen

Uses

helps prevent sunburn

if used as directed with other sun protection measures (see Directions), decreases the risk of skin cancer and early skin aging caused by the sun

Keep out of reach of children.If product is swallowed, get medical help or contact a Poison Control Center right away.

Stop use and ask a doctorif rash occurs

Warnings

For external use only

Do not use on damaged or broken skin

When using this productkeep out of eyes. Rinse with water to remove.

Directions
Apply liberally 15 minutes before sun exposure
Reapply at least every 2 hours
Use a water resistant sunscreen if swimming or sweating
Children under 6 months: Ask a doctor

Sun Protection Measures.Spending time in the sun increases your risk of skin
cancer and early skin aging. To decrease this risk, regularly use a sunscreen
with broad spectrum SPF of 15 or higher and other sun protection measures
including:
limit time in the sun, especially from 10 a.m. - 2 p.m.
wear long-sleeve shirts, pants, hats, and sunglasses

INACTIVE INGREDIENT

Inactive ingredients: Water/Aqua, Butylene Glycol, Glyceryl Stearate, Stearic Acid, Isopropyl Isostearate, Di-PPG-3 Myristyl Ether Adipate, Potassium Cetyl Phosphate, Hydrogenated Palm Glycerides, Cetyl Alcohol, Triethanolamine, Lecithin, Silica, Dimethicone, Polysorbate 20, Hydrolyzed Lupinus Albus (Lupine) Protein, Medicago Sativa (Alfalfa) Seed Extract, DMDM Hydantoin, Xanthan Gum, Biosaccharide Gum-4, Chondrus Crispus (Carrageenan) Extract, Magnesium Aluminum Silicate, Tocopheryl Acetate, Tagetus Erecta (African Marigold) Extract, Ipomoea Batatas Tuber Extract, PEG-4 Laurate, Iodopropynyl Butylcarbamate, Trisodium EDTA [May Contain +/- : Titanium Dioxide/CI 77891, Iron Oxides/CI 77491/CI 77492/CI 77499]